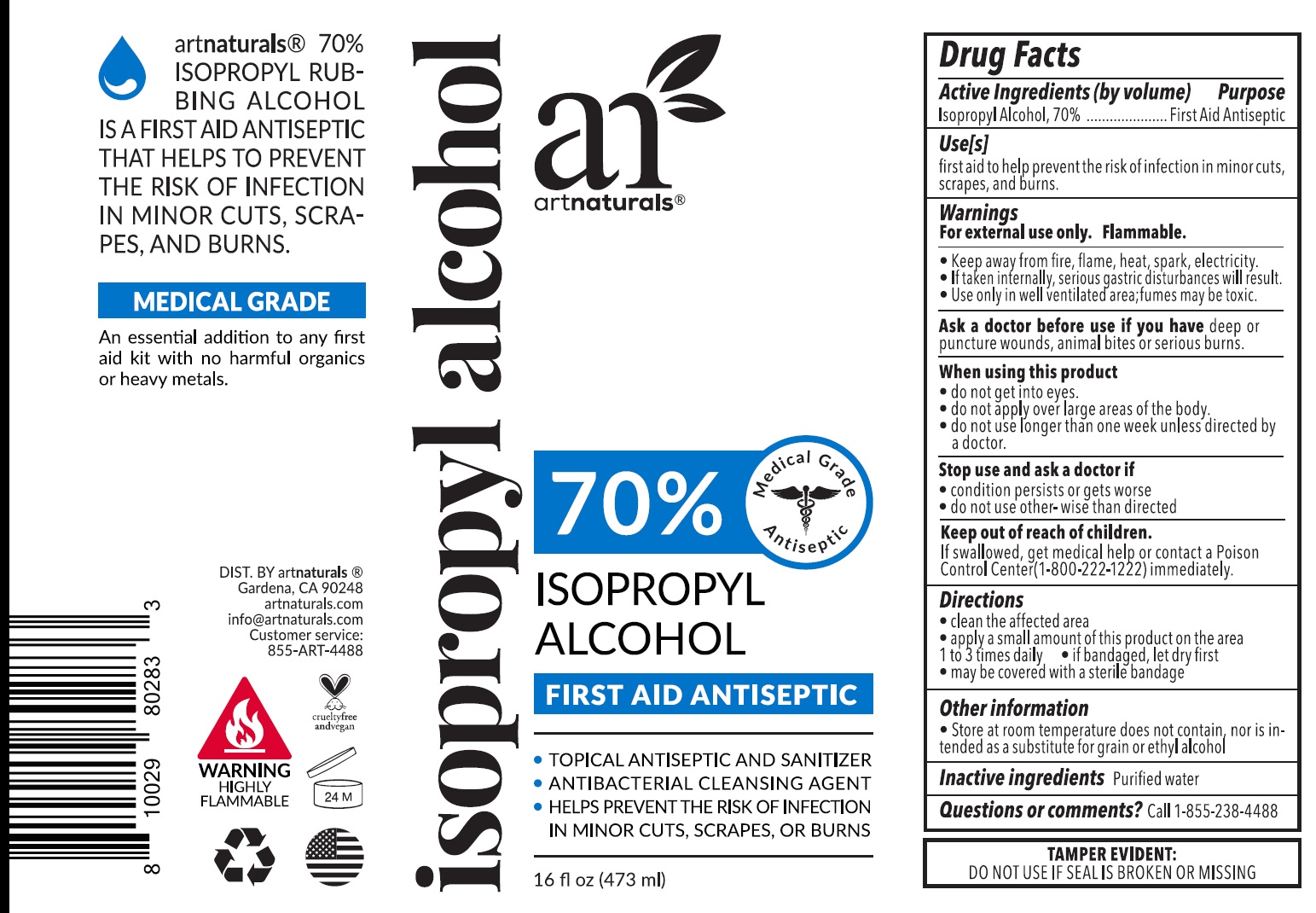 DRUG LABEL: Isopropyl Alcohol 70%
NDC: 78706-001 | Form: LIQUID
Manufacturer: Virgin Scent Inc.
Category: otc | Type: HUMAN OTC DRUG LABEL
Date: 20220721

ACTIVE INGREDIENTS: ISOPROPYL ALCOHOL 0.7 mL/1 mL
INACTIVE INGREDIENTS: WATER

Isopropyl Alcohol 70%

Active Ingredients (by volume)

Isopropyl Alcohol, 70%

Purpose

First Aid Antiseptic

Use[s]

first aid to help prevent the risk of infection in minor cuts, scrapes, and burns.

Warnings

For external use only. Flammable.

- Keep away from fire, flame, heat, spark, electricity.
- If taken internally, serious gastric disturbances will result.
- Use only in well ventilated area; fumes may be toxic.

Ask a doctor before use if you have

deep or puncture wounds, animal bites or serious burns.

When using this product

- do not get into eyes.
- do not apply over large areas of the body.
- do not use longer than week unless directed by a doctor.

Stop use and ask a doctor if

- condition persists or gets worse
- do not use other-wise than directed

Keep out of reach of children.

If swallowed, get medical help or contact a Poison Control Center (1-800-222-1222) immediately.

Directions

- clean the affected area
- apply a small amount of this product on the area 1 to 3 times daily
- if bandaged, let dry first
- may be covered with a sterile bandage

Other information

- Store at room temperature does not contain, nor is intended as a substitute for grain or ethyl alcohol

Inactive ingredients

Purified water

Questions or comments?

Call 1-855-238-4488